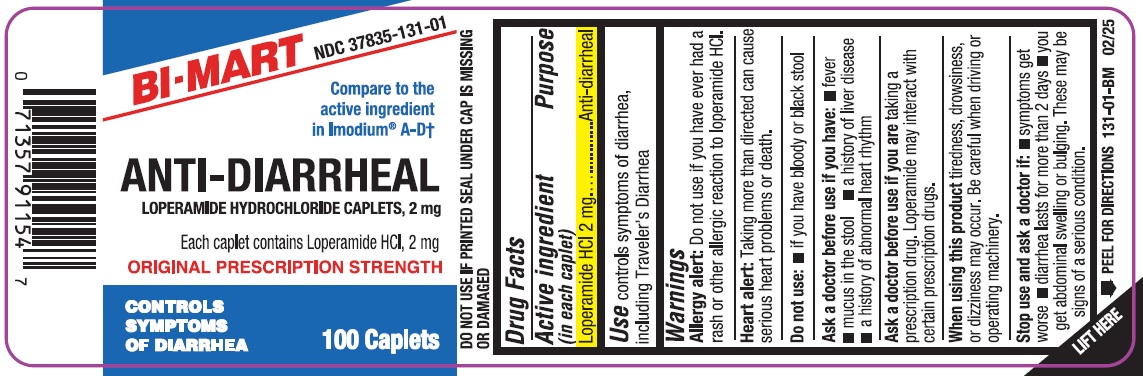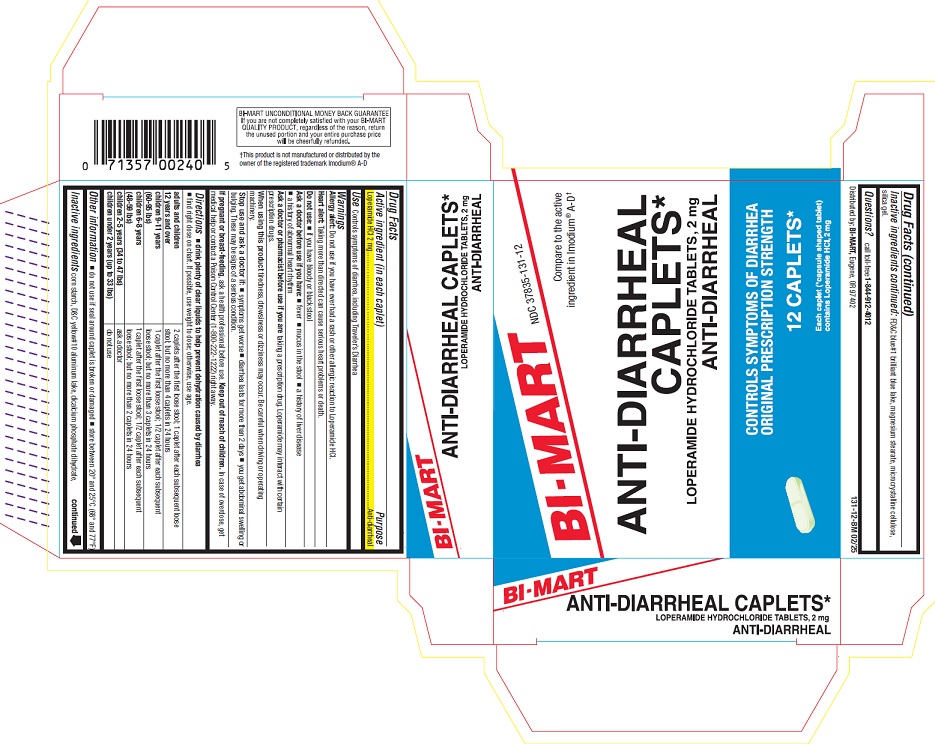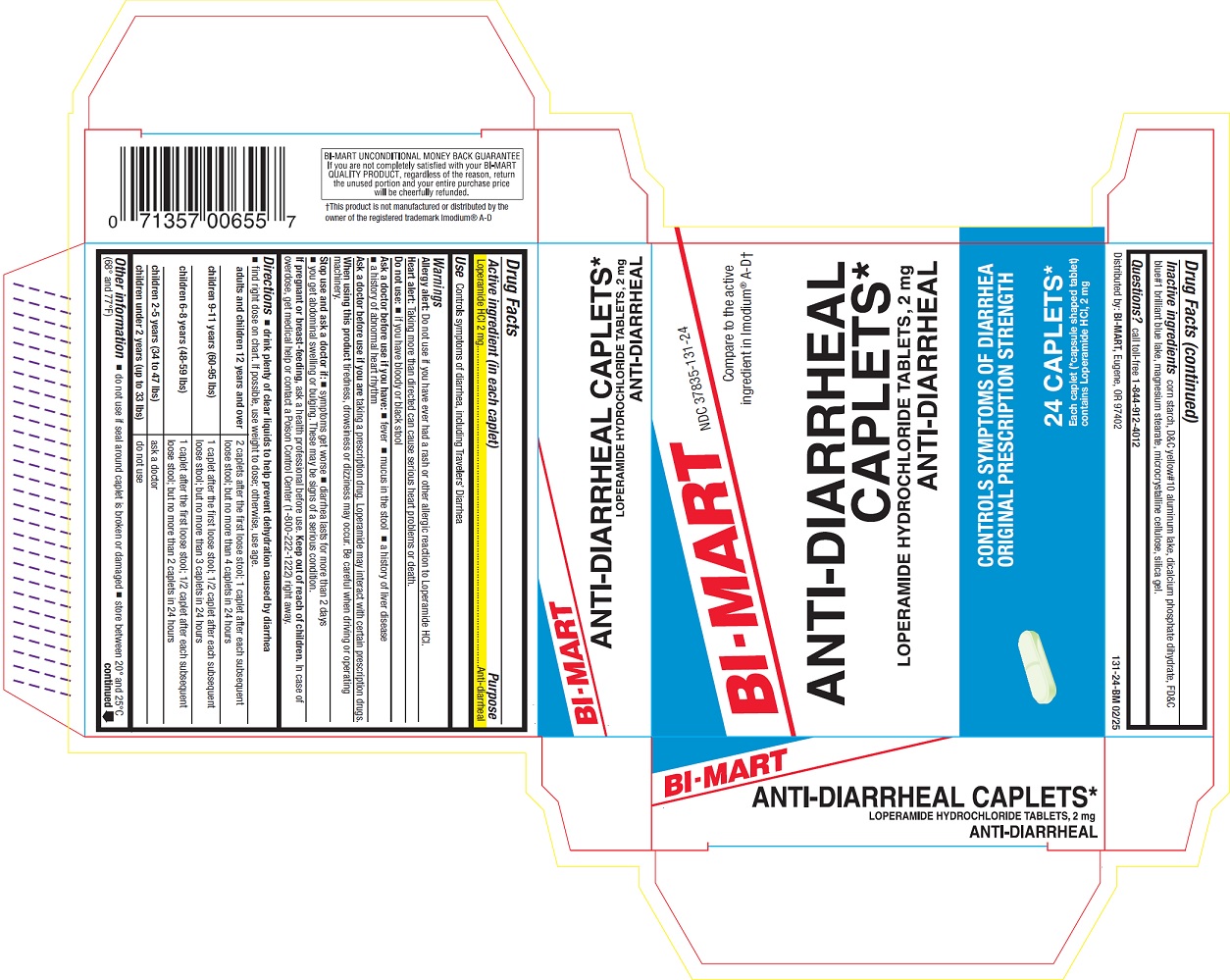 DRUG LABEL: Anti-diarrheal
NDC: 37835-131 | Form: TABLET
Manufacturer: BI-MART
Category: otc | Type: HUMAN OTC DRUG LABEL
Date: 20250501

ACTIVE INGREDIENTS: LOPERAMIDE HYDROCHLORIDE 2 mg/1 1
INACTIVE INGREDIENTS: STARCH, CORN; D&C YELLOW NO. 10 ALUMINUM LAKE; DIBASIC CALCIUM PHOSPHATE DIHYDRATE; FD&C BLUE NO. 1 ALUMINUM LAKE; MAGNESIUM STEARATE; MICROCRYSTALLINE CELLULOSE; SILICON DIOXIDE

Active ingredient (in each caplet)

Loperamide HCl 2 mg

Purpose

Anti-diarrheal

Use

Controls symptoms of diarrhea, including Traveler's Diarrhea

Warnings

Allergy alert: Do not use if you have ever had a rash or other allergic reaction to Loperamide HCl.
Heart alert: Taking more than directed can cause serious heart problems or death.

Do not use

- if you have bloody or black stool.

Ask a doctor before use if you have

- fever
- mucus in the stool
- a history of liver disease
- a history of abnormal heart rhythm

Ask a doctor or pharmacist before use if you are

taking a prescription drug. Loperamide may interact with certain prescription drugs.

When using this product

tiredness, drowsiness or dizziness may occur. Be careful when driving or operating machinery.

Stop use and ask a doctor if

- symptoms get worse
- diarrhea lasts for more than 2 days
- you get abdominal swelling or bulging. These may be signs of a serious condition.

If pregnant or breast-feeding,

ask a health professional before use.

Keep out of reach of children.

In case of overdose, get medical help or contact a Poison Control Center (1-800-222-1222) right away.

Directions

- drink plenty of clear liquids to help prevent dehydration caused by diarrhea
- find right dose on chart. If possible, use weight to dose; otherwise, use age.

adults and children 12 years and over | 2 caplets after the first loose stool; 1 caplet after each subsequent loose stool; but no more than 4 caplets in 24 hours
children 9-11 years; (60-95 lbs) | 1 caplet after the first loose stool; 1/2 caplet after each subsequent loose stool; but no more than 3 caplets in 24 hours
children 6-8 years; (48-59 lbs) | 1 caplet after the first loose stool; 1/2 caplet after each subsequent loose stool; but no more than 2 caplets in 24 hours
children 2-5 years; (34-47 lbs) | ask a doctor
children under 2 years (up to 33 lbs) | do not use

Other information

- do not use if seal around caplet is broken or damaged
- store between 20º and 25ºC (68º and 77ºF)

Inactive ingredients

corn starch, D&C yellow #10 aluminum lake, dicalcium phosphate dihydrate, FD&C blue #1 brilliant blue lake, magnesium stearate, microcrystalline cellulose, silica gel

Questions?

Call toll-free 1-844-912-4012

Principal Display Panel-12 Caplets

NDC 37835-131-12

Compare to active ingredient in Imodium®A-D†

ANTI-DIARRHEAL

CAPLETS*

Loperamide HCl Tablets, 2 mg

ANTI-DIARRHEAL

Controls the symptoms of diarrhea

Original Prescription Strength

12 Caplets*

Each caplet (*capsule shaped tablet contains Loperamide HCl, 2 mg)

†This product is not manufactured or distributed by Kenvue Inc., owner of the registered trademark Imodium®A-D.

Distributed by BI-MART, Eugene, OR 97402

Principal Display Panel-24 Caplets

NDC 37835-131-24

Compare to active ingredient in Imodium®A-D†

ANTI-DIARRHEAL

CAPLETS*

Loperamide HCl Tablets, 2 mg

ANTI-DIARRHEAL

Controls the symptoms of diarrhea

Original Prescription Strength

24 Caplets*

Each caplet (*capsule shaped tablet contains Loperamide HCl, 2 mg)

†This product is not manufactured or distributed by Kenvue Inc., owner of the registered trademark Imodium®A-D.

Distributed by BI-MART, Eugene, OR 97402

Principal Display Panel-100 Caplets

NDC 37835-131-01

Compare to active ingredient in Imodium®A-D†

ANTI-DIARRHEAL

CAPLETS*

Loperamide HCl Tablets, 2 mg

ANTI-DIARRHEAL

Controls the symptoms of diarrhea

Original Prescription Strength

100 Caplets*

Each caplet (*capsule shaped tablet contains Loperamide HCl, 2 mg)

†This product is not manufactured or distributed by Kenvue Inc., owner of the registered trademark Imodium®A-D.

Distributed by BI-MART, Eugene, OR 97402